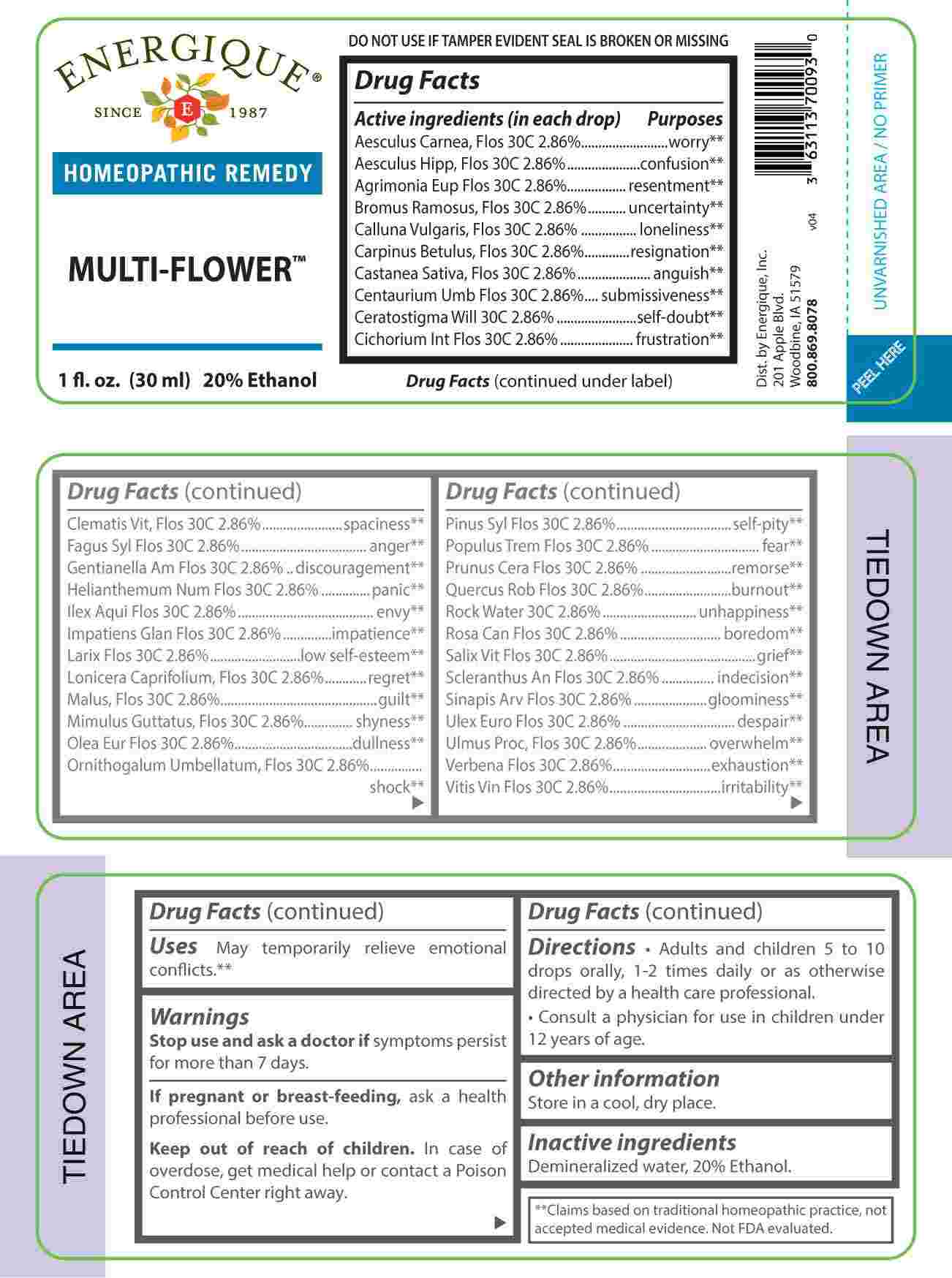 DRUG LABEL: Multi Flower
NDC: 44911-0022 | Form: LIQUID
Manufacturer: Energique, Inc.
Category: homeopathic | Type: HUMAN OTC DRUG LABEL
Date: 20240123

ACTIVE INGREDIENTS: AESCULUS CARNEA FLOWER 30 [hp_C]/1 mL; AESCULUS HIPPOCASTANUM FLOWER 30 [hp_C]/1 mL; AGRIMONIA EUPATORIA FLOWER 30 [hp_C]/1 mL; BROMUS RAMOSUS FLOWER 30 [hp_C]/1 mL; CALLUNA VULGARIS FLOWERING TOP 30 [hp_C]/1 mL; CARPINUS BETULUS FLOWER 30 [hp_C]/1 mL; CASTANEA SATIVA FLOWER 30 [hp_C]/1 mL; CENTAURIUM ERYTHRAEA 30 [hp_C]/1 mL; CERATOSTIGMA WILLMOTTIANUM FLOWER 30 [hp_C]/1 mL; CICHORIUM INTYBUS FLOWER 30 [hp_C]/1 mL; CLEMATIS VITALBA FLOWER 30 [hp_C]/1 mL; FAGUS SYLVATICA FLOWERING TOP 30 [hp_C]/1 mL; GENTIANELLA AMARELLA FLOWER 30 [hp_C]/1 mL; HELIANTHEMUM NUMMULARIUM FLOWER 30 [hp_C]/1 mL; ILEX AQUIFOLIUM FLOWERING TOP 30 [hp_C]/1 mL; IMPATIENS GLANDULIFERA FLOWER 30 [hp_C]/1 mL; LARIX DECIDUA FLOWERING TOP 30 [hp_C]/1 mL; LONICERA CAPRIFOLIUM FLOWER 30 [hp_C]/1 mL; MALUS SYLVESTRIS FLOWER 30 [hp_C]/1 mL; MIMULUS GUTTATUS FLOWERING TOP 30 [hp_C]/1 mL; OLEA EUROPAEA FLOWER 30 [hp_C]/1 mL; ORNITHOGALUM UMBELLATUM 30 [hp_C]/1 mL; PINUS SYLVESTRIS FLOWERING TOP 30 [hp_C]/1 mL; POPULUS TREMULA FLOWERING TOP 30 [hp_C]/1 mL; PRUNUS CERASIFERA FLOWER 30 [hp_C]/1 mL; QUERCUS ROBUR FLOWER 30 [hp_C]/1 mL; WATER 30 [hp_C]/1 mL; ROSA CANINA FLOWER 30 [hp_C]/1 mL; SALIX ALBA FLOWERING TOP 30 [hp_C]/1 mL; SCLERANTHUS ANNUUS FLOWERING TOP 30 [hp_C]/1 mL; SINAPIS ARVENSIS FLOWERING/FRUITING TOP 30 [hp_C]/1 mL; ULEX EUROPAEUS FLOWER 30 [hp_C]/1 mL; ULMUS PROCERA FLOWERING TWIG 30 [hp_C]/1 mL; VERBENA OFFICINALIS FLOWERING TOP 30 [hp_C]/1 mL; VITIS VINIFERA FLOWERING TOP 30 [hp_C]/1 mL
INACTIVE INGREDIENTS: ALCOHOL

DRUG FACTS:

ACTIVE INGREDIENTS:

(in each drop) Aesculus Carnea, Flos 30C 2.86%, Aesculus Hippocastanum, Flos 30C 2.86%, Agrimonia Eupatoria, Flos 30C 2.86%, Bromus Ramosus, Flos 30C 2.86%, Calluna Vulgaris, Flos 30C 2.86%, Carpinus Betulus , Flos 30C 2.86%, Castanea Sativa, Flos 30C 2.86%, Centaurium Umbellatum, Flos 30C 2.86%, Ceratostigma Willmottianum, Flos 30C 2.86%, Cichorium Intybus, Flos 30C 2.86%, Clematis Vitalba, Flos 30C 2.86%, Fagus Sylvatica, Flos 30C 2.86%, Gentianella Amarella, Flos 30C 2.86%, Helianthemum Nummularium, Flos 30C 2.86%, Ilex Aquifolium, Flos 30C 2.86%, Impatiens Glandulifera, Flos 30C 2.86%, Larix Decidua, Flos 30C 2.86%, Lonicera Caprifolium, Flos 30C 2.86%, Malus Pumila, Flos 30C 2.86%, Mimulus Guttatus, Flos 30C 2.86%, Olea Europaea, Flos 30C 2.86%, Ornithogalum Umbellatum, Flos 30C 2.86%, Pinus Sylvestris, Flos 30C 2.86%, Populus Tremula, Flos 30C 2.86%, Prunus Cerasifera, Flos 30C 2.86%, Quercus Robur, Flos 30C2.86%, Rock Water 30C 2.86%, Rosa Canina, Flos 30C 2.86%, Salix Vitellina, Flos 30C 2.86%, Scleranthus Annuus, Flos 30C 2.86%, Sinapis Arvensis, Flos 30C 2.86%, Ulex Europaeus, Flos 30C 2.86%, Ulmus Procera, Flos 30C 2.86%, Verbena Officinalis, Flos 30C 2.86%, Vitis Vinifera, Flos 30C 2.86%.

PURPOSE:

Aesculus Carnea, Flos - worry,** Aesculus Hippocastanum, Flos - confusion,** Agrimonia Eupatoria, Flos - resentment,** Bromus Ramosus, Flos - uncertainty,** Calluna Vulgaris, Flos - loneliness,** Carpinus Betulus , Flos - resignation,** Castanea Sativa, Flos - anguish,** Centaurium Umbellatum, Flos - submissiveness,** Ceratostigma Willmottianum, Flos – self-doubt,** Cichorium Intybus, Flos – frustration,** Clematis Vitalba, Flos - spaciness,** Fagus Sylvatica, Flos - anger,** Gentianella Amarella, Flos - discouragement,** Helianthemum Nummularium, Flos - panic,** Ilex Aquifolium, Flos - envy,** Impatiens Glandulifera, Flos - impatience,** Larix Decidua, Flos – low self-esteem,** Lonicera Caprifolium, Flos - regret,** Malus Pumila, Flos - guilt,** Mimulus Guttatus, Flos - shyness,** Olea Europaea, Flos - dullness,** Ornithogalum Umbellatum, Flos - shock,** Pinus Sylvestris, Flos – self-pity,** Populus Tremula, Flos - fear,** Prunus Cerasifera, Flos - remorse,** Quercus Robur, Flos - burnout,** Rock Water - unhappiness,** Rosa Canina, Flos - boredom,** Salix Vitellina, Flos - grief,** Scleranthus Annuus, Flos - indecision,** Sinapis Arvensis, Flos - gloominess,** Ulex Europaeus, Flos - despair,** Ulmus Procera, Flos - overwhelm,** Verbena Officinalis, Flos - exhaustion,** Vitis Vinifera, Flos - irritability.**

**Claims based on traditional homeopathic practice, not accepted medical evidence. Not FDA evaluated.

USES:

May temporarily relieve emotional conflicts.**

**Claims based on traditional homeopathic practice, not accepted medical evidence. Not FDA evaluated.

WARNINGS:

Stop use and ask a doctor if symptoms persist for more than 7 days.

If pregnant or breast-feeding, ask a health professional before use.

Keep out of reach of children. In case of overdose, get medical help or contact a Poison Control Center right away.

DO NOT USE IF TAMPER EVIDENT SEAL IS BROKEN OR MISSING

Store in a cool, dry place.

KEEP OUT OF REACH OF CHILDREN:

In case of overdose, get medical help or contact a Poison Control Center right away.

DIRECTIONS:

• Adults and children 5 to 10 drops orally, 1-2 times daily or as otherwise directed by a health care professional.

• Consult a physician for use in children under 12 years of age.

INACTIVE INGREDIENTS:

Demineralized water, 20% Ethanol.

QUESTIONS:

Dist. by Energique, Inc.

201 Apple Blvd.

Woodbine, IA 51579

800.869.8078

PACKAGE LABEL DISPLAY:

ENERGIQUE

SINCE 1987

HOMEOPATHIC REMEDY

MULTI-FLOWER

1 fl. oz. (30 ml)